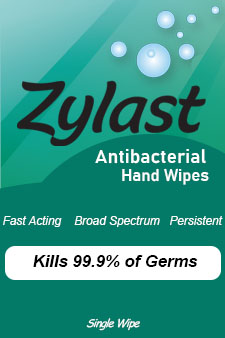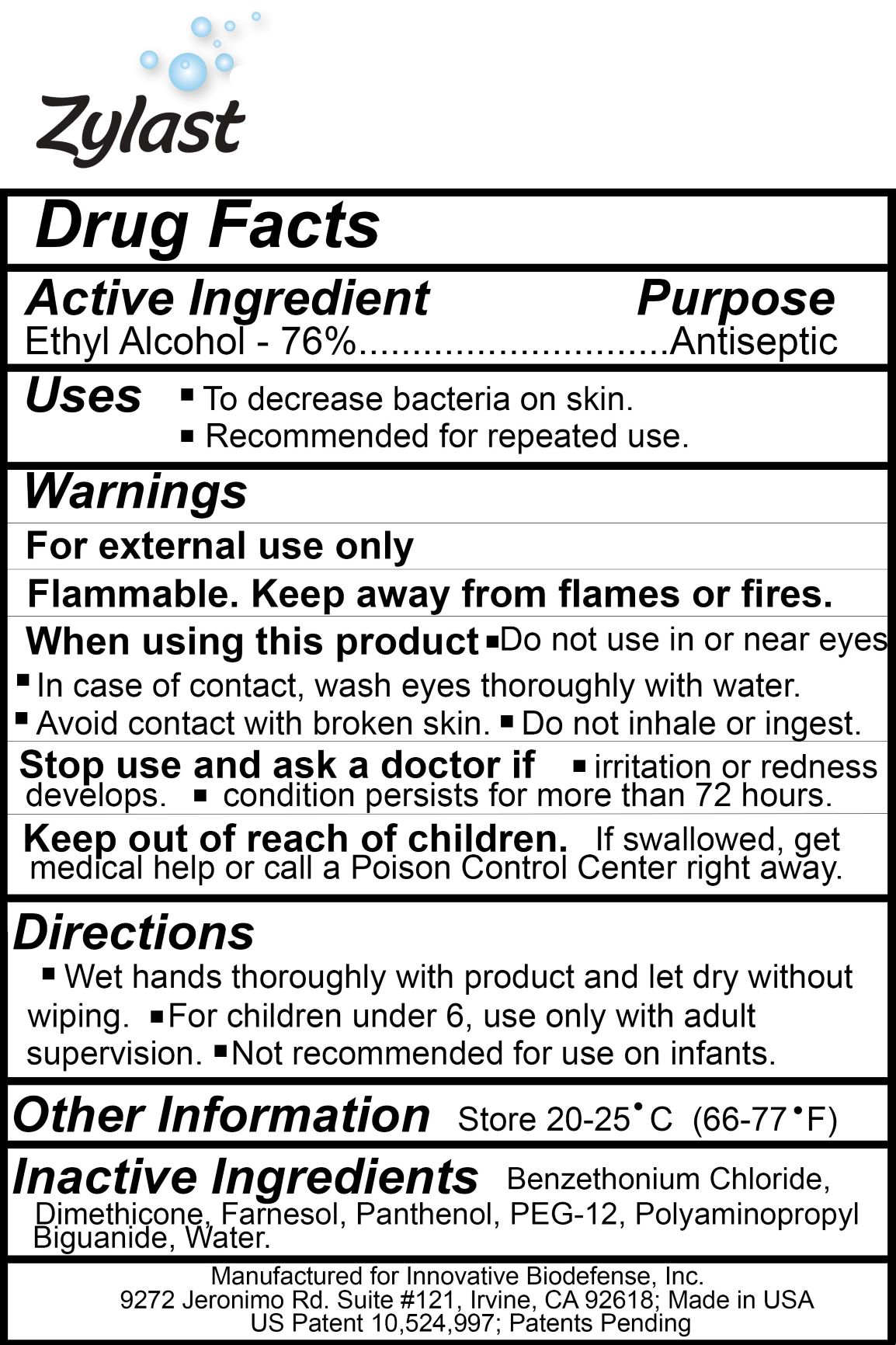 DRUG LABEL: Antiseptic Wipes
NDC: 57362-469 | Form: SWAB
Manufacturer: Westwood Laboratories
Category: otc | Type: HUMAN OTC DRUG LABEL
Date: 20230101

ACTIVE INGREDIENTS: ALCOHOL 76 mL/100 mL
INACTIVE INGREDIENTS: WATER

Zylast Antibacterial Hand Wipes

ACTIVE INGREDIENT

Ethyl Alcohol - 76%

PURPOSE

Antiseptic

INDICATIONS AND USAGE

- To decrease bacteria on skin.
- Recommended for repeated use.

WARNINGS

- For external use only
- Flammable. Keep away from flames or fires.

WHEN USING

- Do not used in or near eyes.
- In case of contact, wash eyes thoroughly with water.
- Avoid contact with broken skin.
- Do not inhale or ingest.

STOP USE

- Irritiation or redness develops.
- Condition persists for more than 72 hours.

KEEP OUT OF REACH OF CHILDREN

If swallowed, get medical help or call a Poison Control Center right away.

DOSAGE AND ADMINISTRATION

- Wet hands thoroughly with product and let dry without wiping.
- For children under 6, use only with adult supervision.
- Not recommended for use on infants.

STORAGE AND HANDLING

Store 20-25*C (66-77*F)

INACTIVE INGREDIENT

Benzethonium Chloride, Dimethicone, Farnesol, Panthenol, PEG-12, Polyaminopropyl Biguanide, Water.

PACKAGE LABEL

Single Wipe Labeling

NDC: 57362-469-18